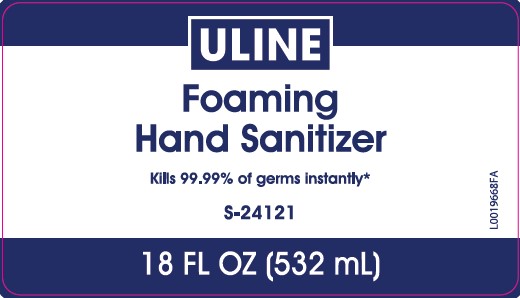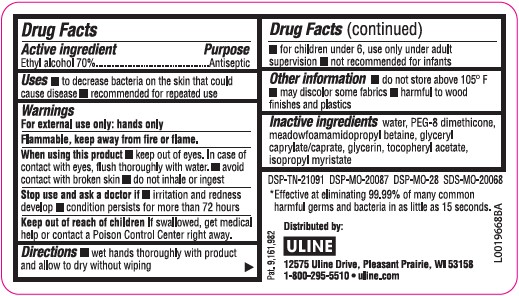 DRUG LABEL: Hand Sanitizer
NDC: 69790-456 | Form: LIQUID
Manufacturer: Uline
Category: otc | Type: HUMAN OTC DRUG LABEL
Date: 20260217

ACTIVE INGREDIENTS: ALCOHOL 70 mL/100 mL
INACTIVE INGREDIENTS: WATER; PEG-8 DIMETHICONE; MEADOWFOAMAMIDOPROPYL BETAINE; GLYCERYL CAPRYLATE/CAPRATE; GLYCERIN; .ALPHA.-TOCOPHEROL ACETATE; ISOPROPYL MYRISTATE

Uline 456.001/456AC
70% Alcohol Foaming Hand Sanitizer

Active ingredient

Ethyl alcohol 70%

Purpose

Antiseptic

Uses

- to decrease bacteria on the skin that could cause disease
- recommended for repeated use

Warnings

For external use only: hands

Flammable. Keep away from fire or flame.

When using this product

- keep out of eyes. In case of contact with eyes, flush thoroughly with water.
- avoid contact with broken skin
- do not inhale or ingest

Stop use and ask a doctor if

- irritation and redness develop
- condition persists for more than 72 hours

Keep out of reach children

If swallowed, get medical help or contact a Poison Control Center right away.

Directions

- wet hands thoroughly with product and allow to dry without wiping
- for children under 6, use only under adult supervision
- not recommended for infants

Other information

- do not store above 105° F
- may discolor some fabrics
- harmful to wood finishes and plastics

Inactive ingredients

water, PEG-8 Dimethicone, meadowfoamamidopropyl betaine, glyceryl caprylate/caprate, glycerin, tocopheryl acetate, isopropyl Myristate

ADVERSE REACTION

*Effective at eliminating 99.99% of many common harmful germs and bacteria in as little as 15 seconds.

Distributed by: ULINE

12575 Uline Drive, Pleasant Prairied, WI 53158

1-800-295-5510 uline.com

DSP-TN-21091 DSP-MO-20087 DSP-MO-28 SDS-MO-20068

principal display panel

ULINE

Foaming

Hand Samitizer

Kills 99.99% of germs instantly*

S-24121

18 FL OZ (532 mL)